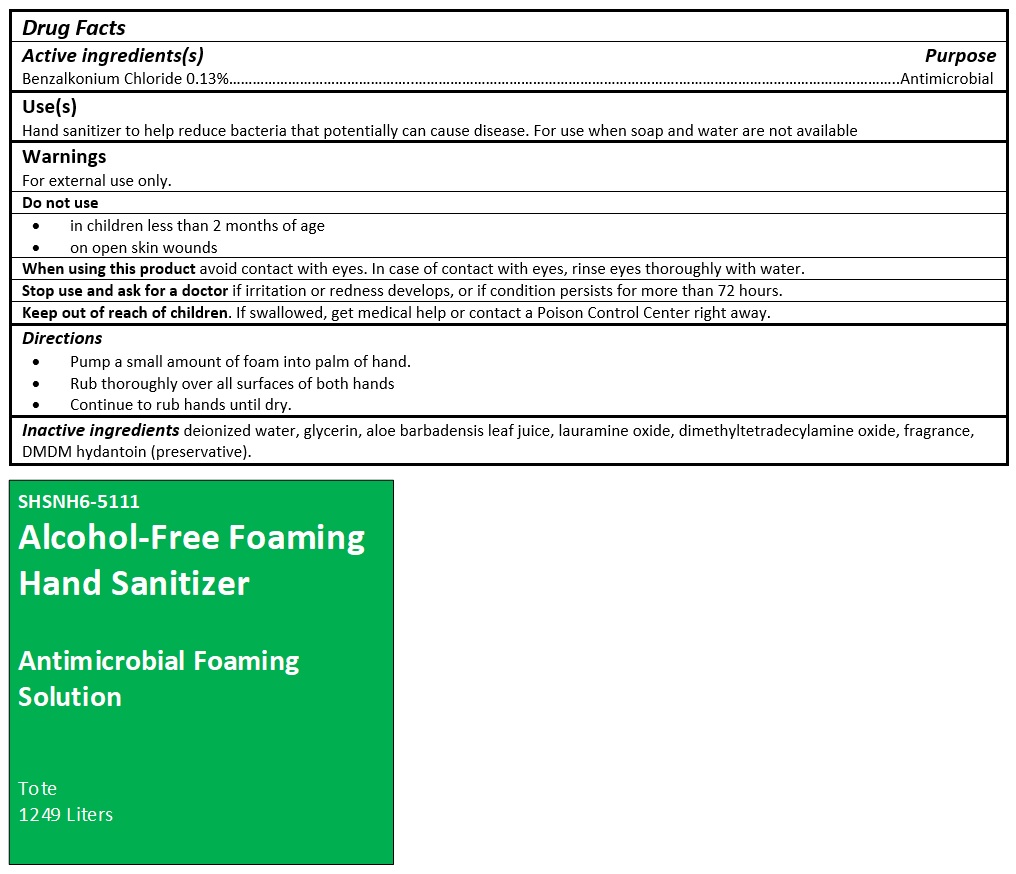 DRUG LABEL: SHSNH6-5111
NDC: 73870-201 | Form: SOLUTION
Manufacturer: Shotwell Hydrogenics, LLC
Category: otc | Type: HUMAN OTC DRUG LABEL
Date: 20201123

ACTIVE INGREDIENTS: BENZALKONIUM CHLORIDE 1.3 g/1 L
INACTIVE INGREDIENTS: WATER; GLYCERIN; ALOE VERA LEAF; LAURAMINE OXIDE; MYRISTAMINE OXIDE; DMDM HYDANTOIN

SHSNH6-5111 Alcohol-Free Foaming Hand Sanitizer Antimicrobial Foaming Solution

Active ingredients(s)

Benzalkonium Chloride 0.13%

Purpose

Antimicrobial

Use(s)

Hand sanitizer to help reduce bacteria that potentially can cause disease. For use when soap and water are not available

Warnings

For external use only.

Do not use

• in children less than 2 months of age

• on open skin wounds

When using this product avoid contact with eyes. In case of contact with eyes, rinse eyes thoroughly with water.

Stop use and ask for a doctor if irritation or redness develops, or if condition persists for more than 72 hours.

Keep out of reach of children. If swallowed, get medical help or contact a Poison Control Center right away.

Directions

• Pump a small amount of foam into palm of hand.

• Rub thoroughly over all surfaces of both hands

• Continue to rub hands until dry.

Inactive ingredients

deionized water, glycerin, aloe barbadensis leaf juice, lauramine oxide, dimethyltetradecylamine oxide, fragrance, DMDM hydantoin (preservative).

Alcohol-Free Foaming Hand Sanitizer

Antimicrobial Foaming Solution